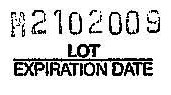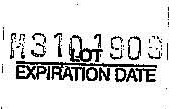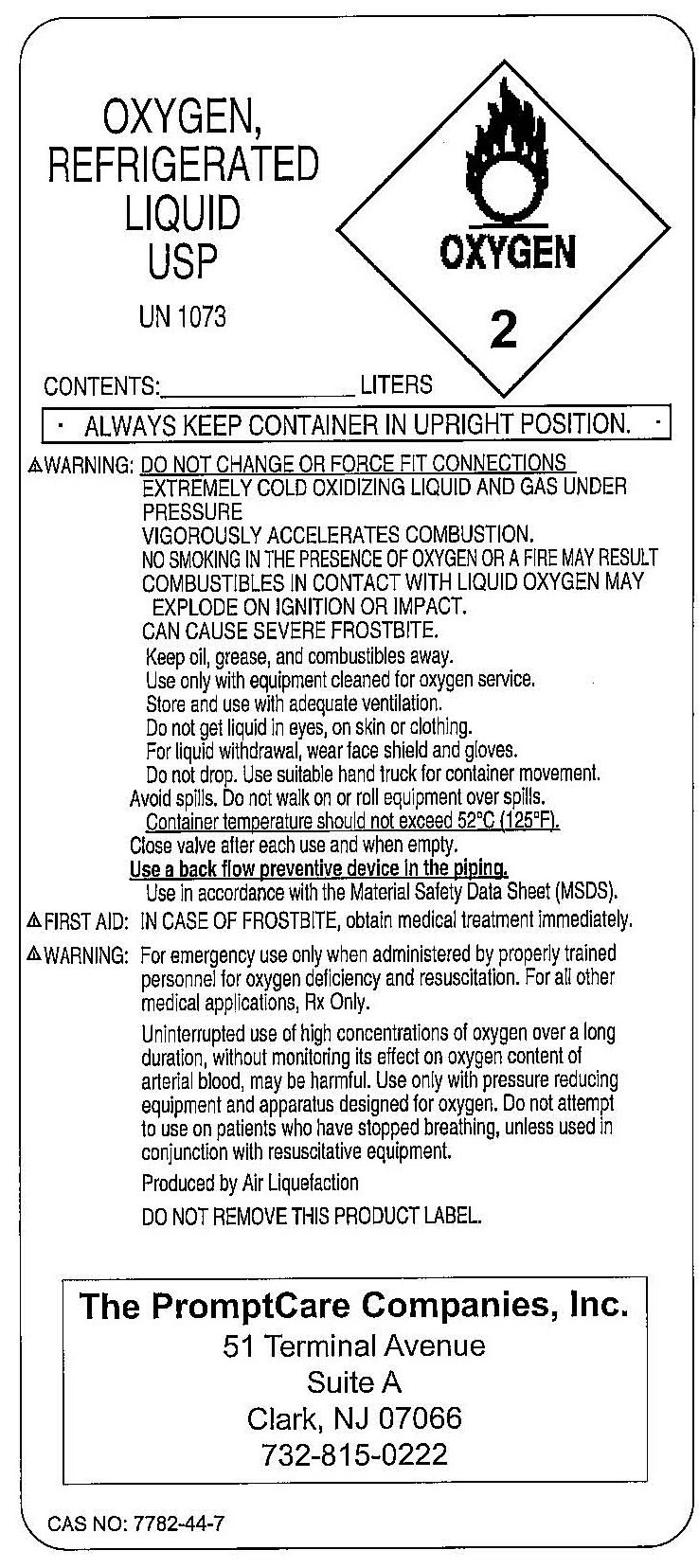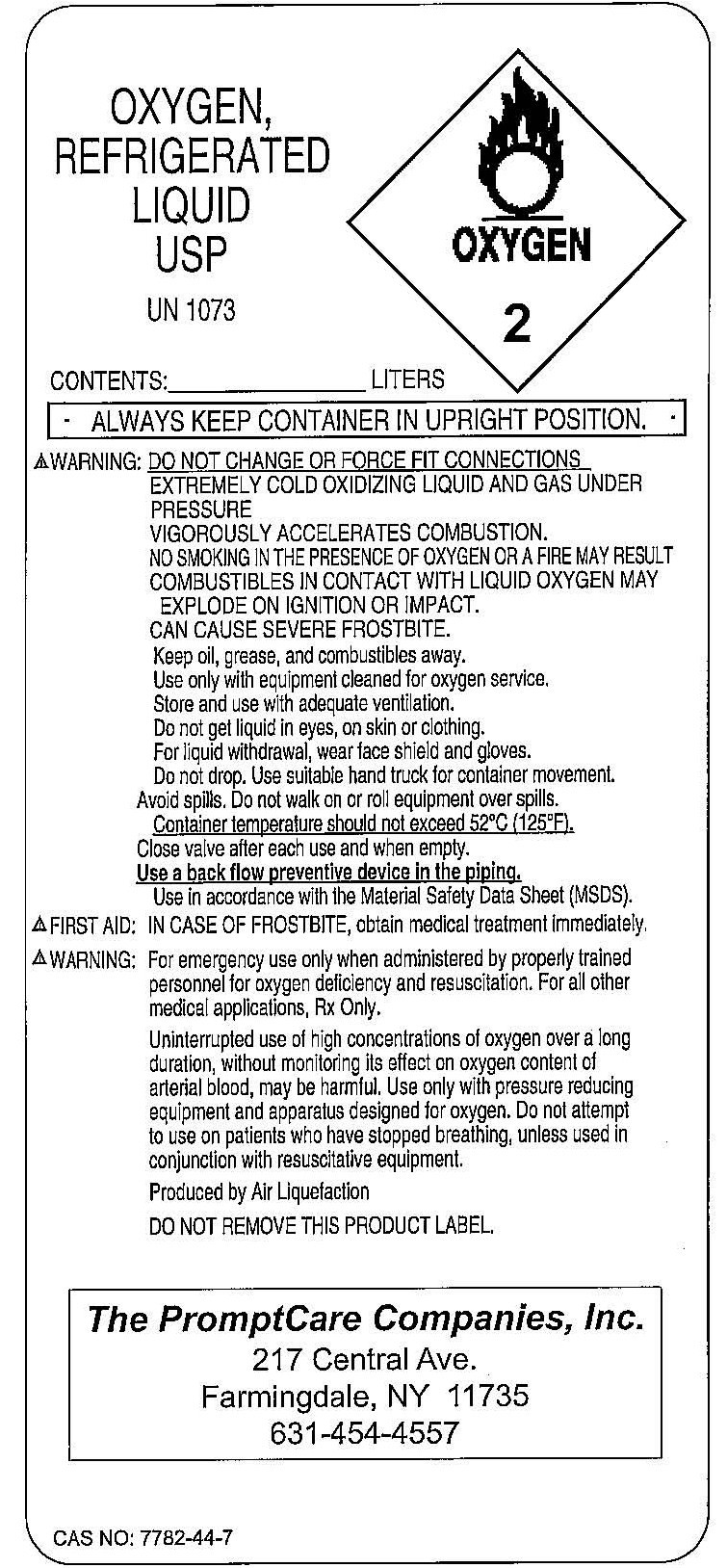 DRUG LABEL: Oxygen
NDC: 57781-1073 | Form: GAS
Manufacturer: Promptcare Companies Inc.
Category: prescription | Type: HUMAN PRESCRIPTION DRUG LABEL
Date: 20091023

ACTIVE INGREDIENTS: Oxygen 99 L/100 L

Oxygen